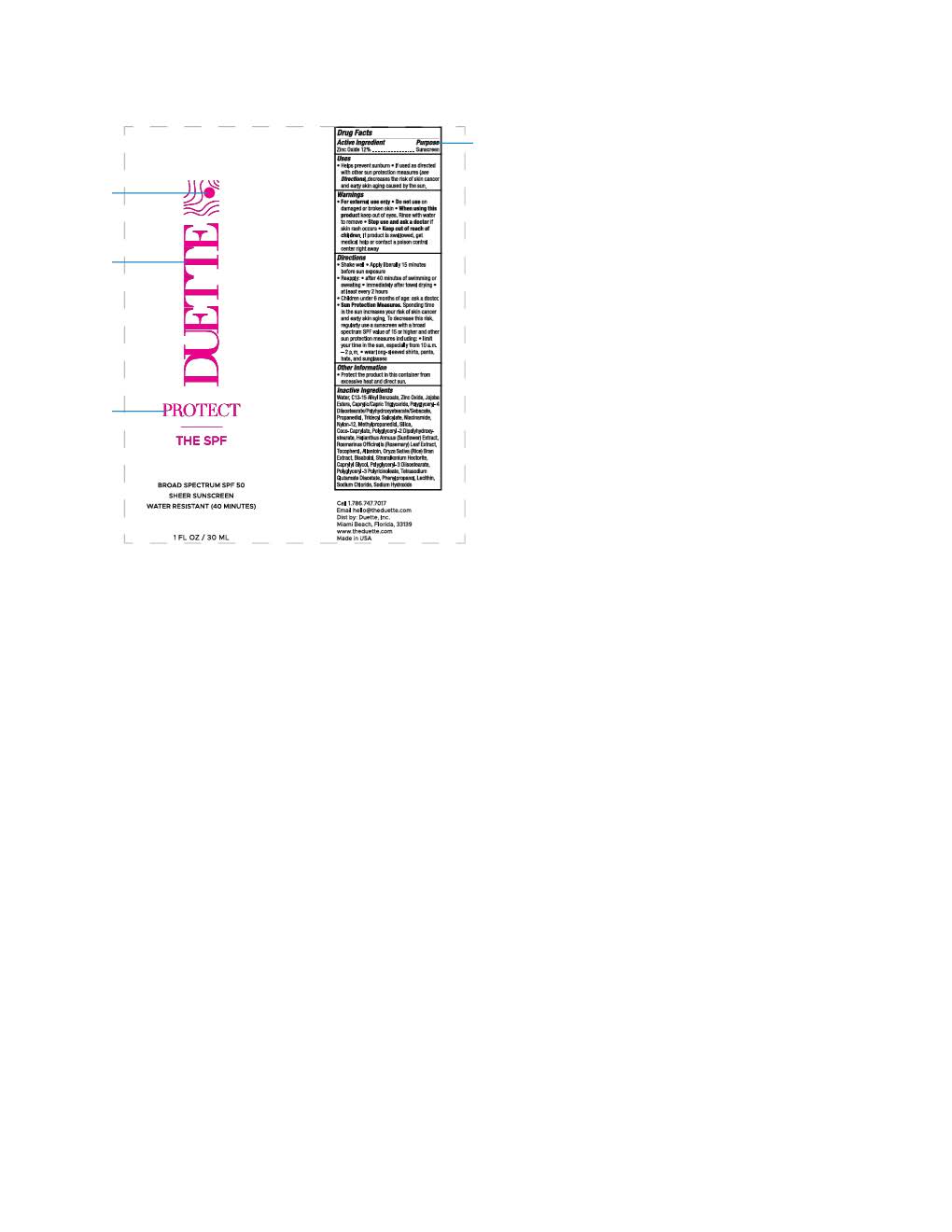 DRUG LABEL: Duette Untinted
NDC: 84123-2033 | Form: LOTION
Manufacturer: Skin Theory Studios
Category: otc | Type: HUMAN OTC DRUG LABEL
Date: 20251106

ACTIVE INGREDIENTS: ZINC OXIDE 132 mg/1 mL
INACTIVE INGREDIENTS: NIACINAMIDE; PROPANEDIOL; TETRASODIUM GLUTAMATE DIACETATE; SODIUM CHLORIDE; POLYGLYCERYL-4 DIISOSTEARATE/POLYHYDROXYSTEARATE/SEBACATE; POLYGLYCERYL-3 DIISOSTEARATE; STEARALKONIUM HECTORITE; WATER; JOJOBA OIL; ORYZA SATIVA WHOLE; TRIDECYL SALICYLATE; SILICON DIOXIDE; TOCOPHEROL; CAPRYLYL GLYCOL; COCO-CAPRYLATE; NYLON-12; PHENYLPROPANOL; HELIANTHUS ANNUUS FLOWERING TOP; LECITHIN, SOYBEAN; METHYLPROPANEDIOL; POLYGLYCERYL-2 DIPOLYHYDROXYSTEARATE; ALLANTOIN; ALKYL (C12-15) BENZOATE; ROSMARINUS OFFICINALIS FLOWER; .ALPHA.-BISABOLOL, (+)-; SODIUM HYDROXIDE

Duette Untinted